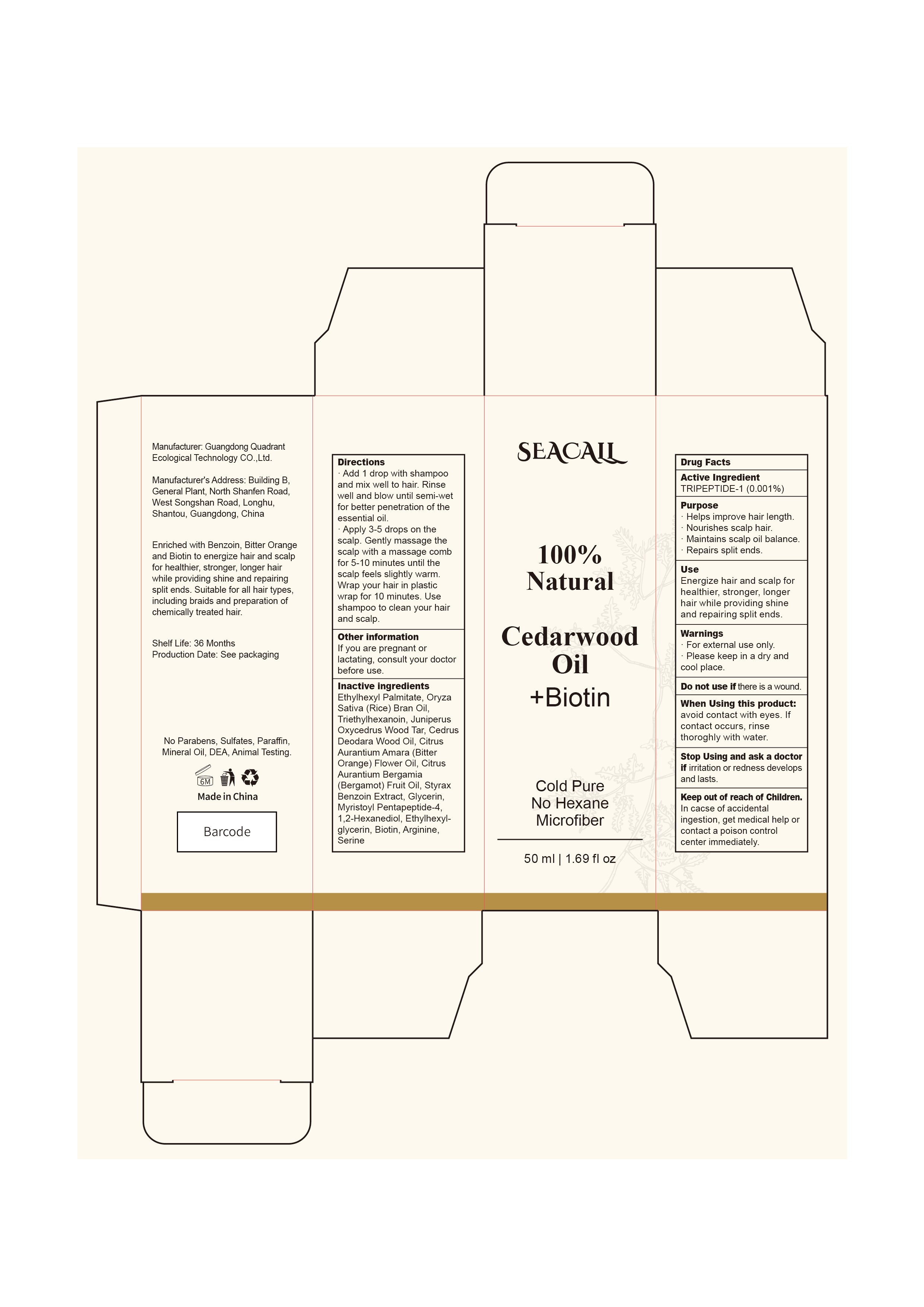 DRUG LABEL: Seacall Natural Cedarwood Oil
NDC: 76986-003 | Form: OIL
Manufacturer: Guangdong Quadrant Ecological Technology Co., Ltd.
Category: otc | Type: HUMAN OTC DRUG LABEL
Date: 20251015

ACTIVE INGREDIENTS: PREZATIDE 0.001 g/100 mL
INACTIVE INGREDIENTS: CEDRUS DEODARA WOOD OIL; ETHYLHEXYL PALMITATE; CITRUS AURANTIUM FLOWER OIL; BERGAMOT OIL; STYRAX BENZOIN WHOLE; BIOTIN; MYRISTOYL PENTAPEPTIDE-4; JUNIPER TAR; RICE BRAN OIL; TRIETHYLHEXANOIN; GLYCERIN; 1,2-HEXANEDIOL; ETHYLHEXYLGLYCERIN; ARGININE; SERINE

76986-003 Active

Active Ingredient

TRIPEPTIDE-1 0.001%

Purpose

· Helps improve hair length.
· Nourishes scalp hair.
· Maintains scalp oil balance.
· Repairs split ends.

Use

Energize hair and scalp for
healthier, stronger, longer
hair while providing shine
and repairing split ends.

Warnings

· For external use only.
· Please keep in a dry and cool place.

Do not use if there is a wound.

When Using

When Using this product:
avoid contact with eyes. If contact occurs, rinse thoroghly with water.

Stop Use

Stop Using and ask a doctor if irritation or redness develops and lasts.

Ask Doctor

Stop Using and ask a doctor if irritation or redness develops and lasts.

Keep Oot Of Reach Of Children

Keep out of reach of Children. In cacse of accidental ingestion, get medical help or contact a poison control center immediately.

Directions

·Add 1 drop with shampoo and mix well to hair. Rinse well and blow until semi-wet for better penetration of the essential oil.
· Apply 3-5 drops on the scalp. Gently massage the scalp with a massage comb for 5-10 minutes until the scalp feels slightly warm.
·Wrap your hair in plastic wrap for 10 minutes. Use shampoo to clean your hair and scalp.

Other information

If you are pregnant or lactating, consult your doctor before use.

Inactive ingredients

Ethylhexyl Palmitate, Oryza Sativa (Rice) Bran Oil, Triethylhexanoin, Juniperus Oxycedrus Wood Tar, Cedrus Deodara Wood Oil, Citrus Aurantium Amara (Bitter Orange) Flower Oil, Citrus Aurantium Bergamia (Bergamot) Fruit Oil, Styrax Benzoin Extract, Glycerin,
Myristoyl Pentapeptide-4, 1,2-Hexanediol, Ethylhexyl glycerin, Biotin, Arginine, Serine